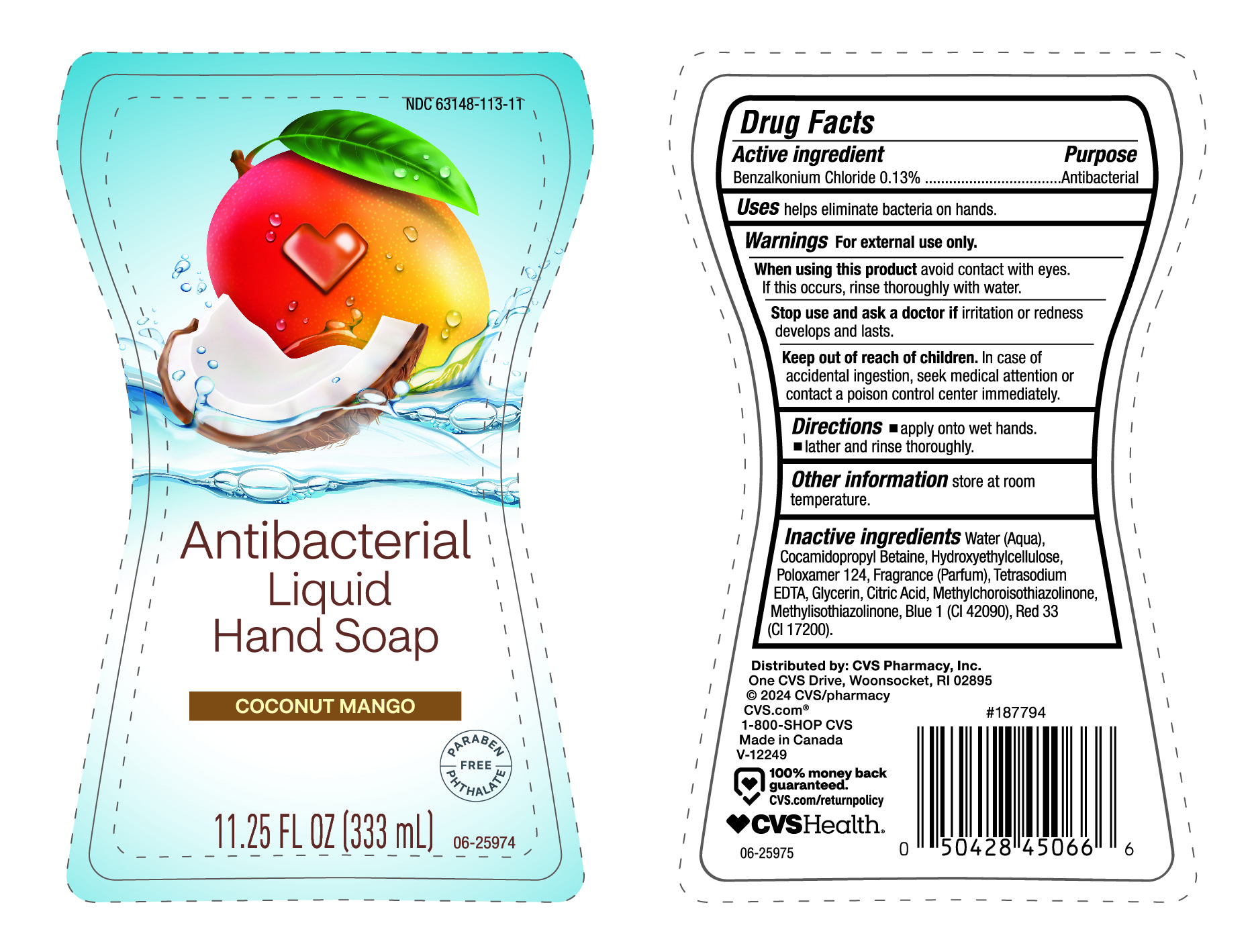 DRUG LABEL: Antibacterial LHS
NDC: 63148-113 | Form: LIQUID
Manufacturer: Apollo Health and Beauty Care
Category: otc | Type: HUMAN OTC DRUG LABEL
Date: 20240221

ACTIVE INGREDIENTS: BENZALKONIUM CHLORIDE 130 mg/100 mL
INACTIVE INGREDIENTS: FRAGRANCE CLEAN ORC0600327; CITRIC ACID MONOHYDRATE; METHYLCHLOROISOTHIAZOLINONE; METHYLISOTHIAZOLINONE; FD&C BLUE NO. 1; D&C RED NO. 33; HYDROXYETHYL CELLULOSE, UNSPECIFIED; EDETATE SODIUM; COCAMIDOPROPYL BETAINE; WATER; GLYCERIN; POLOXAMER 124

CVS Health- Antibacterial Liquid Hand Soap Coconut Mango- NDC- 63148-113-11

Active Ingredient

Benzalkonium Chloride (0.13%)

Purpose

Antibacterial

Uses

Helps eliminate bacteria on hands.

Warnings

For External use only.

When using this product

Avoid contact with eyes. If this occurs, rinse thoroughly with water.

Stop use and ack a doctor if

irritation or redness develops and lasts.

Keep out of reach of children.

In case of accidental ingestion, seek medical attention or contact a poison control center immediately.

Directions

- Apply onto wet hands.
- Lather and rinse thoroughly.

Other Information

Store at room Temperature.

Inactive Ingredients

Water (Aqua), Cocamidopropyl Betaine, Hydroxyethylcellulose, Poloxamer 124, Fragrance (Parfum), Tetrasodium EDTA, Glcerin, Citric Acid, Methylchloroisothiazolinone, Methylisothiazolinone, Blue 1 (CI 42090), Red 33 (CI 17200).